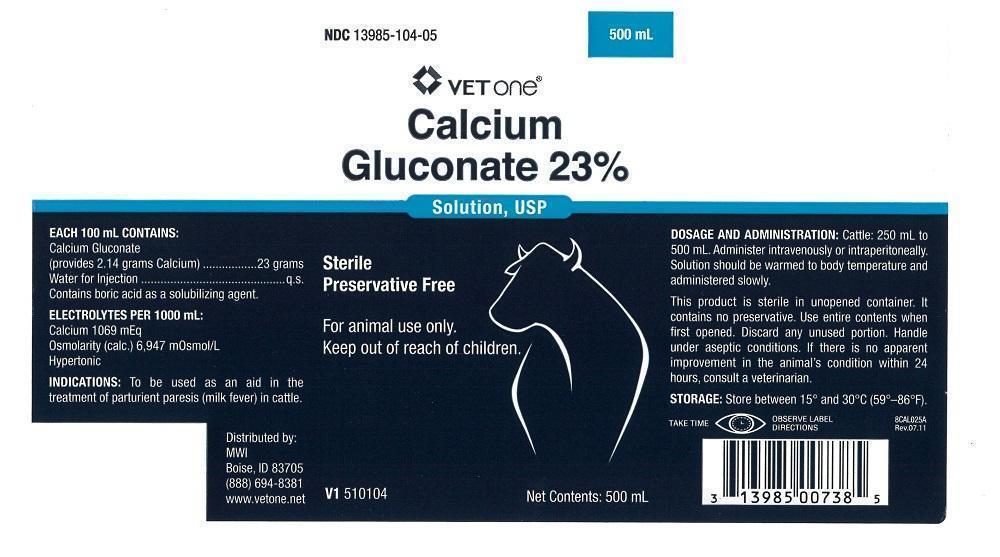 DRUG LABEL: Calcium Gluconate
NDC: 13985-104 | Form: INJECTION
Manufacturer: MWI/VetOne
Category: animal | Type: OTC ANIMAL DRUG LABEL
Date: 20181211

ACTIVE INGREDIENTS: Calcium Gluconate 23 g/100 mL

DESCRIPTION

Calcium Gluconate 23%

Solution, USP

Sterile

Preservative Free

For animal use only.

Keep out of reach of children.

EACH 100 mL CONTAINS:

Calcium Gluconate

(provides 2.14 grams Calcium)..........................23 grams

Water for Injection...................................................q.s.

Contains boric acid as a solubilizing agent.

ELECTROLYTES PER 1000 mL:

Calcium 1069 mEq

Osmoliarity (calc.) 6,947 m0smol/L

Hypertonic

INDICATIONS AND USAGE

INDICATIONS: To be used as an aid in the treatment of parturient paresis (milk fever) in cattle.

DOSAGE AND ADMINISTRATION: Cattle: 250 mL to 500 mL. Administer intravenously or intraperitoneally. Solution should be warmed to body temperature and administered slowly.

This product is sterile in unopened container. It contains no preservative. Use entire contents when first opened. Discard any unused portion. Handle under aseptic conditions. If there is no apparent improvement in the animal's condition within 24 hours, consult a veterinarian.

STORAGE AND HANDLING

STORAGE: Store between 15° and 30°C (59° - 86°F).